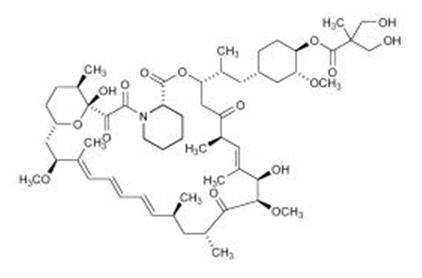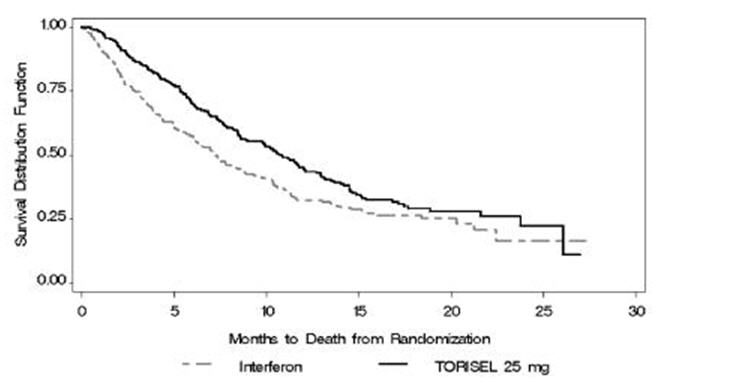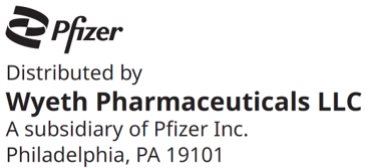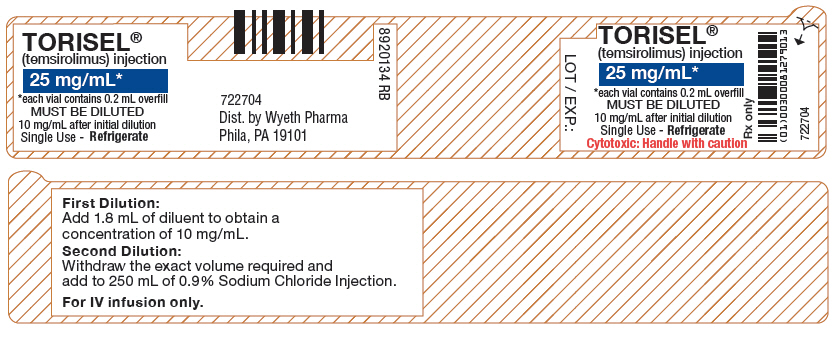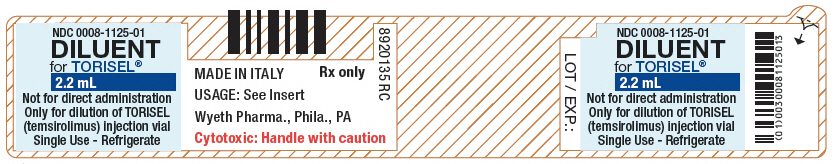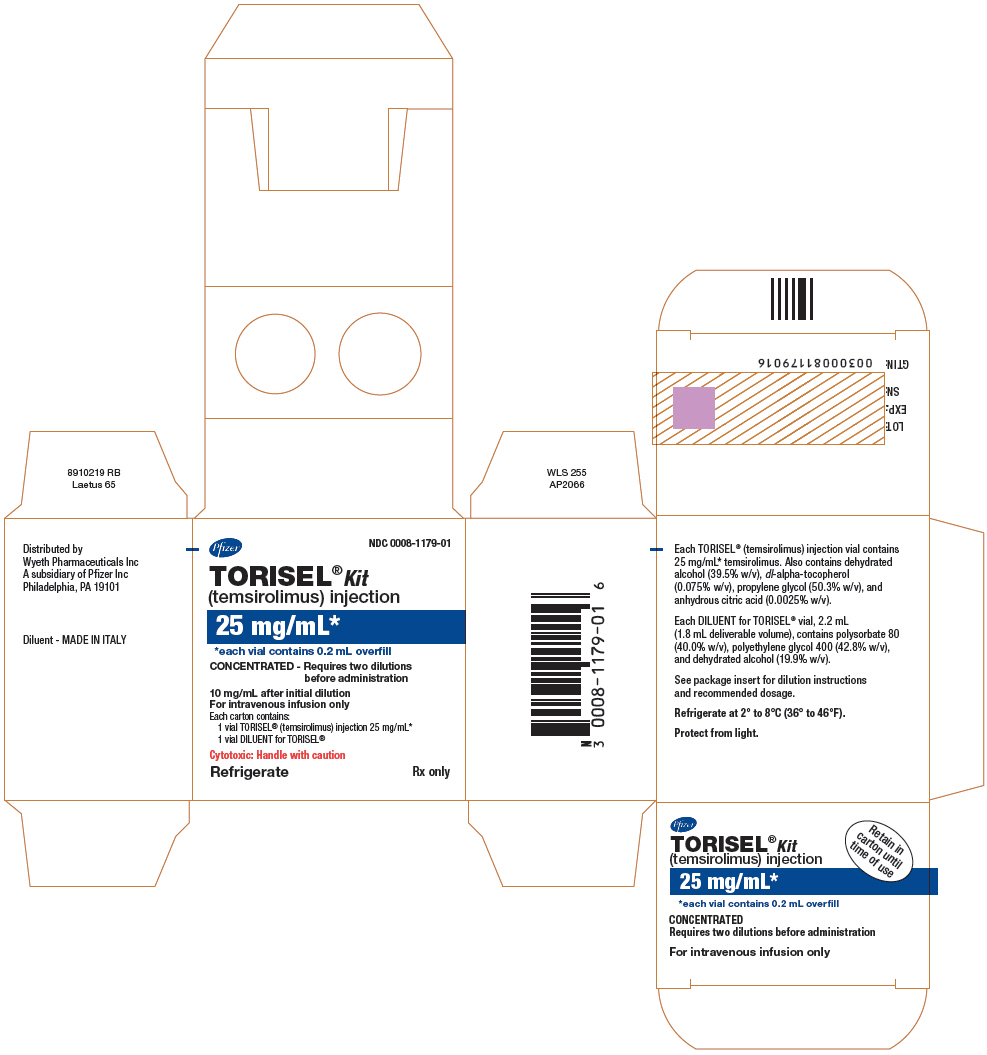 DRUG LABEL: Torisel
NDC: 0008-1179 | Form: KIT | Route: INTRAVENOUS
Manufacturer: Wyeth Pharmaceuticals LLC, a subsidiary of Pfizer Inc.
Category: prescription | Type: HUMAN PRESCRIPTION DRUG LABEL
Date: 20251226

ACTIVE INGREDIENTS: TEMSIROLIMUS 25 mg/1 mL
INACTIVE INGREDIENTS: ANHYDROUS CITRIC ACID 0.025 mg/1 mL; ALCOHOL 394.6 mg/1 mL; PROPYLENE GLYCOL 503.325 mg/1 mL; .ALPHA.-TOCOPHEROL, DL- 0.75 mg/1 mL; POLYSORBATE 80 880 mg/1.8 mL; POLYETHYLENE GLYCOL 400 941 mg/1.8 mL; ALCOHOL 438 mg/1.8 mL

HIGHLIGHTS OF PRESCRIBING INFORMATION

These highlights do not include all the information needed to use TORISEL® safely and effectively. See full prescribing information for TORISEL.
TORISEL Kit (temsirolimus) injection, for intravenous use
Initial U.S. Approval: 2007

1 INDICATIONS AND USAGE

TORISEL® is a kinase inhibitor indicated for the treatment of advanced renal cell carcinoma. (1)

2 DOSAGE AND ADMINISTRATION

- The recommended dose of TORISEL is 25 mg administered as an intravenous infusion over a 30–60 minute period once a week. Treat until disease progression or unacceptable toxicity. (2.1)
- Antihistamine pre-treatment is recommended. (2.2)
- Dose reduction is required in patients with mild hepatic impairment. (2.4)
- TORISEL (temsirolimus) injection vial contents must first be diluted with the enclosed diluent before diluting the resultant solution with 250 mL of 0.9% Sodium Chloride Injection. (2.5)

3 DOSAGE FORMS AND STRENGTHS

TORISEL injection, 25 mg/mL supplied with DILUENT for TORISEL. (3)

4 CONTRAINDICATIONS

TORISEL is contraindicated in patients with bilirubin > 1.5×ULN. (4)

5 WARNINGS AND PRECAUTIONS

- Hypersensitivity/Infusion Reactions (including some life-threatening and rare fatal reactions) can occur early in the first infusion of TORISEL. Patients should be monitored throughout the infusion. (5.1)
- To treat hypersensitivity reactions, stop TORISEL and treat with an antihistamine. TORISEL may be restarted at physician discretion at a slower rate. (5.1)
- Hepatic Impairment: Use caution when treating patients with mild hepatic impairment and reduce dose. (2.4, 5.2)
- Hyperglycemia and hyperlipidemia are likely and may require treatment. Monitor glucose and lipid profiles. (5.3, 5.6)
- Infections may result from immunosuppression. (5.4)
- Monitor for symptoms or radiographic changes of interstitial lung disease (ILD). If ILD is suspected, discontinue TORISEL, and consider use of corticosteroids and/or antibiotics. (5.5)
- Bowel perforation may occur. Evaluate fever, abdominal pain, bloody stools, and/or acute abdomen promptly. (5.7)
- Renal failure, sometimes fatal, has occurred. Monitor renal function at baseline and while on TORISEL. (5.8)
- Due to abnormal wound healing, use TORISEL with caution in the perioperative period. (5.9)
- Proteinuria and nephrotic syndrome may occur. Monitor urine protein prior to the start of TORISEL therapy and periodically thereafter. Discontinue TORISEL in patients with who develop nephrotic syndrome. (5.11)
- Live vaccinations and close contact with those who received live vaccines should be avoided. (5.14)
- Embryo-Fetal Toxicity: Can cause fetal harm. Advise patients of the potential hazard to the fetus and to use effective contraception. (5.15, 8.1, 8.3)
- Elderly patients may be more likely to experience certain adverse reactions, including diarrhea, edema and pneumonia. (5.16)

6 ADVERSE REACTIONS

The most common adverse reactions (incidence ≥30%) are rash, asthenia, mucositis, nausea, edema, and anorexia. The most common laboratory abnormalities (incidence ≥30%) are anemia, hyperglycemia, hyperlipidemia, hypertriglyceridemia, elevated alkaline phosphatase, elevated serum creatinine, lymphopenia, hypophosphatemia, thrombocytopenia, elevated AST, and leukopenia. (6)To report SUSPECTED ADVERSE REACTIONS, contact Wyeth Pharmaceuticals Inc. at 1-800-934-5556 or FDA at 1-800-FDA-1088 or www.fda.gov/medwatch

7 DRUG INTERACTIONS

Strong inducers of CYP3A4/5 and inhibitors of CYP3A4 may affect concentrations of the primary metabolite of TORISEL. If alternatives cannot be used, dose modifications of TORISEL are recommended. (7.1, 7.2, 7.3)

8 USE IN SPECIFIC POPULATIONS

Lactation: Do not breastfeed. (8.2)

FULL PRESCRIBING INFORMATION

1 INDICATIONS AND USAGE

TORISEL is indicated for the treatment of advanced renal cell carcinoma.

2 DOSAGE AND ADMINISTRATION

2.1 Advanced Renal Cell Carcinoma

The recommended dose of TORISEL for advanced renal cell carcinoma is 25 mg administered as an intravenous infusion over a 30 – 60 minute period once a week.

Treatment should continue until disease progression or unacceptable toxicity occurs.

2.2 Premedication

Patients should receive prophylactic intravenous diphenhydramine 25 to 50 mg (or similar antihistamine) approximately 30 minutes before the start of each dose of TORISEL [see Warnings and Precautions (5.1)].

2.3 Dosage Interruption/Adjustment

TORISEL should be held for absolute neutrophil count (ANC) <1,000/mm^3, platelet count <75,000/mm^3, or NCI CTCAE grade 3 or greater adverse reactions. Once toxicities have resolved to grade 2 or less, TORISEL may be restarted with the dose reduced by 5 mg/week to a dose no lower than 15 mg/week.

2.4 Dose Modification Guidelines

Hepatic Impairment: Use caution when treating patients with hepatic impairment. If TORISEL must be given in patients with mild hepatic impairment (bilirubin >1 – 1.5×ULN or AST >ULN but bilirubin ≤ULN), reduce the dose of TORISEL to 15 mg/week. TORISEL is contraindicated in patients with bilirubin >1.5×ULN [see Contraindications (4), Warnings and Precautions (5.2) and Use in Specific Populations (8.7)].

Concomitant Strong CYP3A4 Inhibitors: The concomitant use of strong CYP3A4 inhibitors should be avoided (e.g. ketoconazole, itraconazole, clarithromycin, atazanavir, indinavir, nefazodone, nelfinavir, ritonavir, saquinavir, telithromycin, and voriconazole). Grapefruit juice may also increase plasma concentrations of sirolimus (a major metabolite of temsirolimus) and should be avoided. If patients must be co-administered a strong CYP3A4 inhibitor, based on pharmacokinetic studies, a TORISEL dose reduction to 12.5 mg/week should be considered. This dose of TORISEL is predicted to adjust the AUC to the range observed without inhibitors. However, there are no clinical data with this dose adjustment in patients receiving strong CYP3A4 inhibitors. If the strong inhibitor is discontinued, a washout period of approximately 1 week should be allowed before the TORISEL dose is adjusted back to the dose used prior to initiation of the strong CYP3A4 inhibitor [see Warnings and Precautions (5.12) and Drug Interactions (7.2)].

Concomitant Strong CYP3A4 Inducers: The use of concomitant strong CYP3A4 inducers should be avoided (e.g. dexamethasone, phenytoin, carbamazepine, rifampin, rifabutin, rifampacin, phenobarbital). If patients must be co-administered a strong CYP3A4 inducer, based on pharmacokinetic studies, a TORISEL dose increase from 25 mg/week up to 50 mg/week should be considered. This dose of TORISEL is predicted to adjust the AUC to the range observed without inducers. However, there are no clinical data with this dose adjustment in patients receiving strong CYP3A4 inducers. If the strong inducer is discontinued the temsirolimus dose should be returned to the dose used prior to initiation of the strong CYP3A4 inducer [see Warnings and Precautions (5.12) and Drug Interactions (7.1)].

2.5 Instructions for Preparation

TORISEL is a cytotoxic drug. Follow applicable special handling and disposal procedures^1.

TORISEL must be stored under refrigeration at 2°–8°C (36°–46°F) and protected from light. During handling and preparation of admixtures, TORISEL should be protected from excessive room light and sunlight. Parenteral drug products should be inspected visually for particulate matter and discoloration prior to administration, whenever solution and container permit.

In order to minimize the patient exposure to the plasticizer DEHP (di-2-ethylhexyl phthalate), which may be leached from PVC infusion bags or sets, the final TORISEL dilution for infusion should be stored in bottles (glass, polypropylene) or plastic bags (polypropylene, polyolefin) and administered through polyethylene-lined administration sets.

TORISEL 25 mg/mL injection must be diluted with the supplied diluent before further dilution in 0.9% Sodium Chloride Injection, USP.

Please note that both the TORISEL injection and diluent vials contain an overfill to ensure the recommended volume can be withdrawn.

Follow this two-step dilution process in an aseptic manner.

Step 1:

DILUTION OF TORISEL INJECTION 25 MG/ML WITH SUPPLIED DILUENT

- Each Vial of TORISEL (temsirolimus) must first be mixed with 1.8 mL of the enclosed diluent. The resultant solution contains 30 mg/3 mL (10 mg/mL).
- Mix well by inversion of the vial. Allow sufficient time for the air bubbles to subside. The solution should be clear to slightly turbid, colorless to light-yellow solution, essentially free from visual particulates.

The concentrate-diluent mixture is stable below 25ºC for up to 24 hours.

Step 2:

DILUTION OF CONCENTRATE-DILUENT MIXTURE WITH 0.9% SODIUM CHLORIDE INJECTION, USP

- Withdraw precisely the required amount of concentrate-diluent mixture containing temsirolimus 10 mg/mL as prepared in Step 1 from the vial (i.e., 2.5 mL for a temsirolimus dose of 25 mg) and further dilute into an infusion bag containing 250 mL of 0.9% Sodium Chloride Injection, USP.
- Mix by inversion of the bag or bottle, avoiding excessive shaking, as this may cause foaming.

The resulting solution should be inspected visually for particulate matter and discoloration prior to administration. The admixture of TORISEL in 0.9% Sodium Chloride Injection, USP should be protected from excessive room light and sunlight.

2.6 Administration

- Administration of the final diluted solution should be completed within six hours from the time that TORISEL is first added to 0.9% Solution Chloride Injection, USP.
- TORISEL is administered as an intravenous infusion over a 30- to 60-minute period once weekly. The use of an infusion pump is the preferred method of administration to ensure accurate delivery of the product.
- Appropriate administration materials should be composed of glass, polyolefin, or polyethylene to avoid excessive loss of product and diethylhexylpthalate (DEHP) extraction. The administration materials should consist of non-DEHP, non-polyvinylchloride (PVC) tubing with appropriate filter. In the case when a PVC administration set has to be used, it should not contain DEHP. An in-line polyethersulfone filter with a pore size of not greater than 5 microns is recommended for administration to avoid the possibility of particles bigger than 5 microns being infused. If the administration set available does not have an in-line filter incorporated, a polyethersulfone filter should be added at the set (i.e., an end-filter) before the admixture reaches the vein of the patient. Different end-filters can be used, ranging in filter pore size from 0.2 microns up to 5 microns. The use of both an in-line and end-filter is not recommended.
- TORISEL, when diluted, contains polysorbate 80, which is known to increase the rate of DEHP extraction from PVC. This should be considered during the preparation and administration of TORISEL, including storage time elapsed when in direct contact with PVC following constitution.

Compatibilities and Incompatibilities

Undiluted TORISEL injection should not be added directly to aqueous infusion solutions. Direct addition of TORISEL injection to aqueous solutions will result in precipitation of drug. Always combine TORISEL injection with DILUENT for TORISEL before adding to infusion solutions. It is recommended that TORISEL be administered in 0.9% Sodium Chloride Injection after combining with diluent. The stability of TORISEL in other infusion solutions has not been evaluated. Addition of other drugs or nutritional agents to admixtures of TORISEL in 0.9% Sodium Chloride Injection has not been evaluated and should be avoided. Temsirolimus is degraded by both acids and bases, and thus combinations of temsirolimus with agents capable of modifying solution pH should be avoided.

3 DOSAGE FORMS AND STRENGTHS

TORISEL (temsirolimus) is supplied as a kit consisting of the following:

TORISEL (temsirolimus) injection (25 mg/mL). The TORISEL vial contains temsirolimus at a concentration of 25 mg/mL. The vial contains an overfill of 0.2 mL to ensure the ability to withdraw the recommended dose.

DILUENT for TORISEL. The DILUENT vial includes a deliverable volume of 1.8 mL. This vial contains an overfill in order to ensure that the appropriate volume can be withdrawn.

4 CONTRAINDICATIONS

TORISEL is contraindicated in patients with bilirubin >1.5×ULN [see Warnings and Precautions (5.2)].

5 WARNINGS AND PRECAUTIONS

5.1 Hypersensitivity/Infusion Reactions

Hypersensitivity/infusion reactions, including but not limited to flushing, chest pain, dyspnea, hypotension, apnea, loss of consciousness, hypersensitivity and anaphylaxis, have been associated with the administration of temsirolimus. These reactions can occur very early in the first infusion, but may also occur with subsequent infusions. Patients should be monitored throughout the infusion and appropriate supportive care should be available. Temsirolimus infusion should be interrupted in all patients with severe infusion reactions and appropriate medical therapy administered.

TORISEL should be used with caution in persons with known hypersensitivity to temsirolimus or its metabolites (including sirolimus), polysorbate 80, or to any other component (including the excipients) of TORISEL.

An H1 antihistamine should be administered to patients before the start of the intravenous temsirolimus infusion. TORISEL should be used with caution in patients with known hypersensitivity to an antihistamine, or patients who cannot receive an antihistamine for other medical reasons.

If a patient develops a hypersensitivity reaction during the TORISEL infusion, the infusion should be stopped and the patient should be observed for at least 30 to 60 minutes (depending on the severity of the reaction). At the discretion of the physician, treatment may be resumed with the administration of an H1-receptor antagonist (such as diphenhydramine), if not previously administered [see Dosage and Administration (2.2)], and/or an H2-receptor antagonist (such as intravenous famotidine 20 mg or intravenous ranitidine 50 mg) approximately 30 minutes before restarting the TORISEL infusion. The infusion may then be resumed at a slower rate (up to 60 minutes).

A benefit-risk assessment should be done prior to the continuation of temsirolimus therapy in patients with severe or life-threatening reactions.

5.2 Hepatic Impairment

The safety and pharmacokinetics of TORISEL were evaluated in a dose escalation phase 1 study in 110 patients with normal or varying degrees of hepatic impairment. Patients with baseline bilirubin >1.5×ULN experienced greater toxicity than patients with baseline bilirubin ≤1.5×ULN when treated with TORISEL. The overall frequency of ≥ grade 3 adverse reactions and deaths, including deaths due to progressive disease, were greater in patients with baseline bilirubin >1.5×ULN due to increased risk of death [see Contraindications (4)].

Use caution when treating patients with mild hepatic impairment. Concentrations of temsirolimus and its metabolite sirolimus were increased in patients with elevated AST or bilirubin levels. If TORISEL must be given in patients with mild hepatic impairment (bilirubin >1 – 1.5×ULN or AST >ULN but bilirubin ≤ULN), reduce the dose of TORISEL to 15 mg/week [see Dosage and Administration (2.4)].

5.3 Hyperglycemia/Glucose Intolerance

The use of TORISEL is likely to result in increases in serum glucose. In the phase 3 trial, 89% of patients receiving TORISEL had at least one elevated serum glucose while on treatment, and 26% of patients reported hyperglycemia as an adverse event. This may result in the need for an increase in the dose of, or initiation of, insulin and/or oral hypoglycemic agent therapy. Serum glucose should be tested before and during treatment with TORISEL. Patients should be advised to report excessive thirst or any increase in the volume or frequency of urination.

5.4 Infections

The use of TORISEL may result in immunosuppression. Patients should be carefully observed for the occurrence of infections, including opportunistic infections [see Adverse Reactions (6.1)].

Pneumocystis jiroveci pneumonia (PJP), including fatalities, has been reported in patients who received temsirolimus. This may be associated with concomitant use of corticosteroids or other immunosuppressive agents. Prophylaxis of PJP should be considered when concomitant use of corticosteroids or other immunosuppressive agents are required.

5.5 Interstitial Lung Disease

Cases of interstitial lung disease, some resulting in death, occurred in patients who received TORISEL. Some patients were asymptomatic, or had minimal symptoms, with infiltrates detected on computed tomography scan or chest radiograph. Others presented with symptoms such as dyspnea, cough, hypoxia, and fever. Some patients required discontinuation of TORISEL and/or treatment with corticosteroids and/or antibiotics, while some patients continued treatment without additional intervention. Patients should be advised to report promptly any new or worsening respiratory symptoms.

It is recommended that patients undergo baseline radiographic assessment by lung computed tomography scan or chest radiograph prior to the initiation of TORISEL therapy. Follow such assessments periodically, even in the absence of clinical respiratory symptoms.

It is recommended that patients be followed closely for occurrence of clinical respiratory symptoms. If clinically significant respiratory symptoms develop, consider withholding TORISEL administration until after recovery of symptoms and improvement of radiographic findings related to pneumonitis. Empiric treatment with corticosteroids and/or antibiotics may be considered. Opportunistic infections such as PJP should be considered in the differential diagnosis. For patients who require use of corticosteroids, prophylaxis of PJP may be considered.

5.6 Hyperlipidemia

The use of TORISEL is likely to result in increases in serum triglycerides and cholesterol. In the phase 3 trial, 87% of patients receiving TORISEL had at least one elevated serum cholesterol value and 83% had at least one elevated serum triglyceride value. This may require initiation, or increase in the dose, of lipid-lowering agents. Serum cholesterol and triglycerides should be tested before and during treatment with TORISEL.

5.7 Bowel Perforation

Cases of fatal bowel perforation occurred in patients who received TORISEL. These patients presented with fever, abdominal pain, metabolic acidosis, bloody stools, diarrhea, and/or acute abdomen. Patients should be advised to report promptly any new or worsening abdominal pain or blood in their stools.

5.8 Renal Failure

Cases of rapidly progressive and sometimes fatal acute renal failure not clearly related to disease progression occurred in patients who received TORISEL. Some of these cases were not responsive to dialysis.

5.9 Wound Healing Complications

Use of TORISEL has been associated with abnormal wound healing. Therefore, caution should be exercised with the use of TORISEL in the perioperative period.

5.10 Intracerebral Hemorrhage

Patients with central nervous system tumors (primary CNS tumor or metastases) and/or receiving anticoagulation therapy may be at an increased risk of developing intracerebral bleeding (including fatal outcomes) while receiving TORISEL.

5.11 Proteinuria and Nephrotic syndrome

Proteinuria (including cases of nephrotic syndrome) has occurred in patients treated with TORISEL. Monitor urine protein prior to the start of TORISEL therapy and periodically thereafter. Discontinue TORISEL in patients who develop nephrotic syndrome.

5.12 Co-administration with Inducers or Inhibitors of CYP3A Metabolism

Agents Inducing CYP3A Metabolism:

Strong inducers of CYP3A4/5 such as dexamethasone, carbamazepine, phenytoin, phenobarbital, rifampin, rifabutin, and rifampacin may decrease exposure of the active metabolite, sirolimus. If alternative treatment cannot be administered, a dose adjustment should be considered. St. John's Wort may decrease TORISEL plasma concentrations unpredictably. Patients receiving TORISEL should not take St. John's Wort concomitantly [see Dosage and Administration (2.4) and Drug Interactions (7.1)].

Agents Inhibiting CYP3A Metabolism:

Strong CYP3A4 inhibitors such as atazanavir, clarithromycin, indinavir, itraconazole, ketoconazole, nefazodone, nelfinavir, ritonavir, saquinavir, and telithromycin may increase blood concentrations of the active metabolite sirolimus. If alternative treatments cannot be administered, a dose adjustment should be considered [see Dosage and Administration (2.4) and Drug Interactions (7.2)].

5.13 Concomitant use of TORISEL with sunitinib

The combination of TORISEL and sunitinib resulted in dose-limiting toxicity. Dose-limiting toxicities (Grade 3/4 erythematous maculopapular rash, and gout/cellulitis requiring hospitalization) were observed in two out of three patients treated in the first cohort of a phase 1 study at doses of TORISEL 15 mg IV per week and sunitinib 25 mg oral per day (Days 1–28 followed by a 2-week rest).

5.14 Vaccinations

The use of live vaccines and close contact with those who have received live vaccines should be avoided during treatment with TORISEL. Examples of live vaccines are: intranasal influenza, measles, mumps, rubella, oral polio, BCG, yellow fever, varicella, and TY21a typhoid vaccines.

5.15 Embryo-Fetal Toxicity

Based on findings in animal studies and its mechanism of action, TORISEL can cause fetal harm when administered to a pregnant woman. In animal reproduction studies, daily oral administration of temsirolimus to pregnant animals during organogenesis caused adverse embryo-fetal effects in rats and rabbits at approximately 0.04 and 0.12 times the AUC in patients at the recommended human dose, respectively. Advise pregnant women and females of reproductive potential of the potential risk to a fetus. Advise females of reproductive potential to use effective contraception during treatment with TORISEL and for 3 months after the last dose. Advise males with female partners of reproductive potential to use effective contraception during treatment with TORISEL and for 3 months after the last dose [see Clinical Pharmacology (12.1) and Use in Specific Populations (8.1, 8.3)].

5.16 Elderly Patients

Based on the results of a phase 3 study, elderly patients may be more likely to experience certain adverse reactions including diarrhea, edema, and pneumonia [see Use in Specific Populations (8.5)].

6 ADVERSE REACTIONS

The following serious adverse reactions have been associated with TORISEL in clinical trials and are discussed in greater detail in other sections of the label [see Warnings and Precautions (5)].

- Hypersensitivity/Infusion Reactions [see Warnings and Precautions (5.1)]
- Hepatic Impairment [see Warnings and Precautions (5.2)]
- Hyperglycemia/Glucose Intolerance [see Warnings and Precautions (5.3)]
- Infections [see Warnings and Precautions (5.4)]
- Interstitial Lung Disease [see Warnings and Precautions (5.5)]
- Hyperlipidemia [see Warnings and Precautions (5.6)]
- Bowel Perforation [see Warnings and Precautions (5.7)]
- Renal Failure [see Warnings and Precautions (5.8)]
- Wound Healing Complications [see Warnings and Precautions (5.9)]
- Intracerebral Hemorrhage [see Warnings and Precautions (5.10)]

The most common (≥30%) adverse reactions observed with TORISEL are rash, asthenia, mucositis, nausea, edema, and anorexia. The most common (≥30%) laboratory abnormalities observed with TORISEL are anemia, hyperglycemia, hyperlipidemia, hypertriglyceridemia, lymphopenia, elevated alkaline phosphatase, elevated serum creatinine, hypophosphatemia, thrombocytopenia, elevated AST, and leukopenia.

6.1 Clinical Trials Experience

Because clinical trials are conducted under widely varying conditions, the adverse reaction rates observed cannot be directly compared to rates in other trials and may not reflect the rates observed in clinical practice.

In the phase 3 randomized, open-label study of interferon alfa (IFN-α) alone, TORISEL alone, and TORISEL and IFN-α, a total of 616 patients were treated. Two hundred patients received IFN-α weekly, 208 received TORISEL 25 mg weekly, and 208 patients received a combination of TORISEL and IFN-α weekly [see Clinical Studies (14)].

Treatment with the combination of TORISEL 15 mg and IFN-α was associated with an increased incidence of multiple adverse reactions and did not result in a significant increase in overall survival when compared with IFN-α alone.

Table 1 shows the percentage of patients experiencing treatment emergent adverse reactions. Reactions reported in at least 10% of patients who received TORISEL 25 mg alone or IFN-α alone are listed. Table 2 shows the percentage of patients experiencing selected laboratory abnormalities. Data for the same adverse reactions and laboratory abnormalities in the IFN-α alone arm are shown for comparison:

Table 1 – Adverse Reactions Reported in at Least 10% of Patients Who Received 25 mg IV TORISEL or IFN-α in the Randomized Trial
Adverse Reaction | TORISEL 25 mg n = 208 |  | IFN-α n = 200
Adverse Reaction | All Grades [Common Toxicity Criteria for Adverse Events (CTCAE), Version 3.0.] n (%) | Grades 3&4 n (%) | All Grades n (%) | Grades 3&4 n (%)
General disorders
Asthenia | 106 (51) | 23 (11) | 127 (64) | 52 (26)
Edema [Includes edema, facial edema, and peripheral edema] | 73 (35) | 7 (3) | 21 (11) | 1 (1)
Pain | 59 (28) | 10 (5) | 31 (16) | 4 (2)
Pyrexia | 50 (24) | 1 (1) | 99 (50) | 7 (4)
Weight Loss | 39 (19) | 3 (1) | 50 (25) | 4 (2)
Headache | 31 (15) | 1 (1) | 30 (15) | 0 (0)
Chest Pain | 34 (16) | 2 (1) | 18 (9) | 2 (1)
Chills | 17 (8) | 1 (1) | 59 (30) | 3 (2)
Gastrointestinal disorders
Mucositis [Includes aphthous stomatitis, glossitis, mouth ulceration, mucositis, and stomatitis] | 86 (41) | 6 (3) | 19 (10) | 0 (0)
Anorexia | 66 (32) | 6 (3) | 87 (44) | 8 (4)
Nausea | 77 (37) | 5 (2) | 82 (41) | 9 (5)
Diarrhea | 56 (27) | 3 (1) | 40 (20) | 4 (2)
Abdominal Pain | 44 (21) | 9 (4) | 34 (17) | 3 (2)
Constipation | 42 (20) | 0 (0) | 36 (18) | 1 (1)
Vomiting | 40 (19) | 4 (2) | 57 (29) | 5 (3)
Infections
Infections [Includes infections not otherwise specified (NOS) and the following infections that occurred infrequently as distinct entities: abscess, bronchitis, cellulitis, herpes simplex, and herpes zoster] | 42 (20) | 6 (3) | 19 (10) | 4 (2)
Urinary tract infection [Includes cystitis, dysuria, hematuria, urinary frequency, and urinary tract infection] | 31 (15) | 3 (1) | 24 (12) | 3 (2)
Pharyngitis | 25 (12) | 0 (0) | 3 (2) | 0 (0)
Rhinitis | 20 (10) | 0 (0) | 4 (2) | 0 (0)
Musculoskeletal and connective tissue disorders
Back Pain | 41 (20) | 6 (3) | 28 (14) | 7 (4)
Arthralgia | 37 (18) | 2 (1) | 29 (15) | 2 (1)
Myalgia | 16 (8) | 1 (1) | 29 (15) | 2 (1)
Respiratory, thoracic and mediastinal disorders
Dyspnea | 58 (28) | 18 (9) | 48 (24) | 11 (6)
Cough | 53 (26) | 2 (1) | 29 (15) | 0 (0)
Epistaxis | 25 (12) | 0 (0) | 7 (4) | 0 (0)
Skin and subcutaneous tissue disorders
Rash [Includes eczema, exfoliative dermatitis, maculopapular rash, pruritic rash, pustular rash, rash (NOS), and vesiculobullous rash] | 97 (47) | 10 (5) | 14 (7) | 0 (0)
Pruritus | 40 (19) | 1 (1) | 16 (8) | 0 (0)
Nail Disorder | 28 (14) | 0 (0) | 1 (1) | 0 (0)
Dry Skin | 22 (11) | 1 (1) | 14 (7) | 0 (0)
Acne | 21 (10) | 0 (0) | 2 (1) | 0 (0)
Nervous system disorders
Dysgeusia [Includes taste loss and taste perversion] | 41 (20) | 0 (0) | 17 (9) | 0 (0)
Insomnia | 24 (12) | 1 (1) | 30 (15) | 0 (0)
Depression | 9 (4) | 0 (0) | 27 (14) | 4 (2)

The following selected adverse reactions were reported less frequently (<10%).

Gastrointestinal Disorders – Gastrointestinal hemorrhage (1%), rectal hemorrhage (1%).

Eye Disorders – Conjunctivitis (including lacrimation disorder) (8%).

Immune System – Angioneurotic edema-type reactions (including delayed reactions occurring two months following initiation of therapy) have been observed in some patients who received TORISEL and ACE inhibitors concomitantly.

Infections – Pneumonia (8%), upper respiratory tract infection (7%), wound infection/post-operative wound infection (1%), sepsis (1%).

General Disorders and Administration Site Conditions - Diabetes mellitus (5%).

Respiratory, Thoracic and Mediastinal Disorders – Pleural effusion (4%).

Vascular – Hypertension (7%), venous thromboembolism (including deep vein thrombosis and pulmonary embolus [including fatal outcomes]) (2%), thrombophlebitis (1%), pericardial effusion (1%).

Nervous System Disorders – Convulsion (1%).

Table 2 – Incidence of Selected Laboratory Abnormalities in Patients Who Received 25 mg IV TORISEL or IFN-α in the Randomized Trial
Laboratory Abnormality | TORISEL 25 mg n = 208 |  | IFN-α n = 200
Laboratory Abnormality | All Grades [NCI CTC version 3.0] n (%) | Grades 3&4 n (%) | All Grades n (%) | Grades 3&4 n (%)
Any | 208 (100) | 162 (78) | 195 (98) | 144 (72)
Hematology
Hemoglobin Decreased | 195 (94) | 41 (20) | 180 (90) | 43 (22)
Lymphocytes Decreased [Grade 1 toxicity may be under-reported for lymphocytes and neutrophils] | 110 (53) | 33 (16) | 106 (53) | 48 (24)
Neutrophils Decreased | 39 (19) | 10 (5) | 58 (29) | 19 (10)
Platelets Decreased | 84 (40) | 3 (1) | 51 (26) | 0 (0)
Leukocytes Decreased | 67 (32) | 1 (1) | 93 (47) | 11 (6)
Chemistry
Alkaline Phosphatase Increased | 141 (68) | 7 (3) | 111 (56) | 13 (7)
AST Increased | 79 (38) | 5 (2) | 103 (52) | 14 (7)
Creatinine Increased | 119 (57) | 7 (3) | 97 (49) | 2 (1)
Glucose Increased | 186 (89) | 33 (16) | 128 (64) | 6 (3)
Phosphorus Decreased | 102 (49) | 38 (18) | 61 (31) | 17 (9)
Total Bilirubin Increased | 16 (8) | 2 (1) | 25 (13) | 4 (2)
Total Cholesterol Increased | 181 (87) | 5 (2) | 95 (48) | 2 (1)
Triglycerides Increased | 173 (83) | 92 (44) | 144 (72) | 69 (35)
Potassium Decreased | 43 (21) | 11 (5) | 15 (8) | 0 (0)

6.2 Post-marketing and Other Clinical Experience

The following adverse reactions have been identified during post approval use of TORISEL. Because these reactions are reported voluntarily from a population of uncertain size, it is not always possible to readily estimate their frequency or establish a causal relationship to drug exposure.

The following adverse reactions have been observed in patients receiving temsirolimus: angioedema, rhabdomyolysis, Stevens-Johnson Syndrome, complex regional pain syndrome (reflex sympathetic dystrophy), pancreatitis, cholecystitis, and cholelithiasis.

There are also post-marketing reports of temsirolimus extravasations resulting in swelling, pain, warmth, and erythema.

7 DRUG INTERACTIONS

7.1 Agents Inducing CYP3A Metabolism

Co-administration of TORISEL with rifampin, a potent CYP3A4/5 inducer, had no significant effect on temsirolimus Cmax (maximum concentration) and AUC (area under the concentration versus the time curve) after intravenous administration, but decreased sirolimus Cmax by 65% and AUC by 56% compared to TORISEL treatment alone. If alternative treatment cannot be administered, a dose adjustment should be considered [see Dosage and Administration (2.4)].

7.2 Agents Inhibiting CYP3A Metabolism

Co-administration of TORISEL with ketoconazole, a potent CYP3A4 inhibitor, had no significant effect on temsirolimus Cmax or AUC; however, sirolimus AUC increased 3.1-fold, and Cmax increased 2.2-fold compared to TORISEL alone. If alternative treatment cannot be administered, a dose adjustment should be considered [see Dosage and Administration (2.4)].

7.3 Angioedema with ACE inhibitors and Calcium Channel Blockers

Angioedema has been reported in patients taking mammalian target of rapamycin (mTOR) inhibitors in combination with ramipril and/or amlodipine. Monitor patients for signs and symptoms of angioedema when temsirolimus is given concomitantly with angiotensin converting enzyme (ACE) inhibitors (e.g., ramipril) or calcium channel blockers (CCB) (e.g., amlodipine).

8 USE IN SPECIFIC POPULATIONS

8.1 Pregnancy

Risk Summary

Based on findings in animal studies and its mechanism of action, temsirolimus can cause fetal harm when administered to a pregnant woman [see Clinical Pharmacology (12.1)]. Although there are no data on the use of TORISEL in pregnant women, there are limited data on the use of sirolimus, the active metabolite of temsirolimus, during pregnancy; however, these data are insufficient to inform a drug-associated risk of adverse developmental outcomes. In animal reproductive studies, oral daily administration of temsirolimus to pregnant rats and rabbits during organogenesis caused adverse embryo-fetal effects at approximately 0.04 and 0.12 times the AUC in patients at the recommended dose, respectively (see Data). Advise pregnant women of the potential hazard to a fetus.

The estimated background risk of major birth defects and miscarriage for the indicated population is unknown. All pregnancies have a background risk of birth defect, loss or other adverse outcomes. In the U.S. general population, the estimated background risk of major birth defects and miscarriage in clinically recognized pregnancies is 2–4% and 15–20%, respectively.

Data

Animal Data

Temsirolimus administered daily as an oral formulation throughout organogenesis caused adverse embryo-fetal effects in rats and rabbits at human sub-therapeutic exposures. Embryo-fetal adverse effects in rats consisted of reduced fetal weight and reduced ossifications, and in rabbits included reduced fetal weight, omphalocele, bifurcated sternabrae, notched ribs, and incomplete ossifications.

In rats, the adverse embryo-fetal effects were observed at the oral dose of 2.7 mg/m^2/day (approximately 0.04-fold the AUC in patients with cancer at the human recommended dose). In rabbits, the adverse embryo-fetal effects were observed at the oral dose of ≥7.2 mg/m^2/day (approximately 0.12-fold the AUC in patients with cancer at the recommended human dose).

8.2 Lactation

Risk Summary

There is no information regarding the presence of TORISEL or its metabolites in human milk, or their effects on the breastfed child or milk production. Trace amounts of sirolimus, the active metabolite of temsirolimus, were present in milk from lactating rats administered sirolimus. Because of the potential for serious adverse reactions in a breastfed child from TORISEL, advise a lactating woman not to breastfeed during treatment with TORISEL and for 3 weeks after the final dose.

8.3 Females and Males of Reproductive Potential

Contraception

Females

TORISEL can cause fetal harm when administered to a pregnant woman [see Use in Specific Population (8.1)]. Advise females of reproductive potential to use effective contraception during treatment with TORISEL and for 3 months after the last dose.

Males

Advise males with partners of reproductive potential to use effective contraception during treatment with TORISEL and for 3 months after the last dose [see Nonclinical Toxicology (13.1)].

Infertility

Based on the findings in animal fertility studies, male and female fertility may be compromised by the treatment with Torisel. It is not known if the effects on fertility in animal studies were reversible [see Nonclinical Toxicology (13.1)].

8.4 Pediatric Use

Limited data are available on the use of temsirolimus in pediatric patients. The effectiveness of temsirolimus in pediatric patients with advanced recurrent/refractory solid tumors has not been established.

TORISEL was studied in 71 patients (59 patients ages 1 to 17 years and 12 patients ages 18 to 21 years) with relapsed/refractory solid tumors in a phase 1–2 safety and exploratory pharmacodynamic study.

In phase 1, 19 pediatric patients with advanced recurrent/refractory solid tumors received TORISEL at doses ranging from 10 mg/m^2 to 150 mg/m^2 as a 60-minute intravenous infusion once weekly in three-week cycles.

In phase 2, 52 pediatric patients with recurrent/relapsed neuroblastoma, rhabdomyosarcoma, or high grade glioma received TORISEL at a weekly dose of 75 mg/m^2. One of 19 patients with neuroblastoma achieved a partial response. There were no objective responses in pediatric patients with recurrent/relapsed rhabdomyosarcoma or high grade glioma.

Adverse reactions associated with TORISEL were similar to those observed in adults. The most common adverse reactions (≥20%) in pediatric patients receiving the 75 mg/m^2 dose included thrombocytopenia, infections, asthenia/fatigue, fever, pain, leukopenia, rash, anemia, hyperlipidemia, increased cough, stomatitis, anorexia, increased plasma levels of alanine aminotransferase and aspartate aminotransferase, hypercholesterolemia, hyperglycemia, abdominal pain, headache, arthralgia, upper respiratory infection, nausea and vomiting, neutropenia, hypokalemia, and hypophosphatemia.

Pharmacokinetics:

In phase 1 of the above mentioned pediatric trial, the single dose and multiple dose total systemic exposure (AUC) of temsirolimus and sirolimus were less than dose-proportional over the dose range of 10 to 150 mg/m^2.

In the phase 2 portion, the multiple dose (Day 1, Cycle 2) pharmacokinetics of TORISEL 75 mg/m^2 were characterized in an additional 35 patients ages 28 days to 21 years (median age of 8 years). The geometric mean body surface adjusted clearance of temsirolimus and sirolimus was 9.45 L/h/m^2 and 9.26 L/h/m^2, respectively. The mean elimination half-life of temsirolimus and sirolimus was 31 hours and 44 hours, respectively.

The exposure (AUCss) to temsirolimus and sirolimus was approximately 6-fold and 2-fold higher, respectively than the exposure in adult patients receiving a 25 mg intravenous infusion.

8.5 Geriatric Use

Clinical studies of TORISEL did not include sufficient numbers of subjects aged 65 and older to determine whether they respond differently from younger subjects. Based on the results of a phase 3 study, elderly patients may be more likely to experience certain adverse reactions including diarrhea, edema, and pneumonia [see Warnings and Precautions (5.16)].

8.6 Renal Impairment

No clinical studies were conducted with TORISEL in patients with decreased renal function. Less than 5% of total radioactivity was excreted in the urine following a 25 mg intravenous dose of [^14C]-labeled temsirolimus in healthy subjects. Renal impairment is not expected to markedly influence drug exposure, and no dosage adjustment of TORISEL is recommended in patients with renal impairment.

TORISEL has not been studied in patients undergoing hemodialysis.

8.7 Hepatic Impairment

TORISEL was evaluated in a dose escalation phase 1 study in 110 patients with normal or varying degrees of hepatic impairment as defined by AST and bilirubin levels and patients with liver transplant (Table 3). Patients with moderate and severe hepatic impairment had increased rates of adverse reactions and deaths, including deaths due to progressive disease, during the study (Table 3).

Table 3 – Adverse Reactions in Patients with Advanced Malignancies Plus Normal or Impaired Hepatic Function
Hepatic Function [Hepatic Function Groups: normal = bilirubin and AST ≤ULN; mild = bilirubin >1 – 1.5×ULN or AST >ULN but bilirubin ≤ULN; moderate = bilirubin >1.5 – 3×ULN; severe = bilirubin >3×ULN; liver transplant = any bilirubin and AST.] | TORISEL Dose Range | Adverse Reactions Grade ≥ 3 [Common Terminology Criteria for Adverse Events, version 3.0, including all causality.] n (%) | Death [Includes deaths due to progressive disease and adverse reactions.] n (%)
Normal (n = 25) | 25 – 175 | 20 (80.0) | 2 (8.0)
Mild (n = 39) | 10 – 25 | 32 (82.1) | 5 (12.8)
Moderate (n = 20) | 10 – 25 | 19 (95.0) | 8 (40.0)
Severe (n = 24) | 7.5 – 15 | 23 (95.8) | 13 (54.2)
Liver Transplant (n = 2) | 10 | 1 (50.0) | 0 (0)

TORISEL is contraindicated in patients with bilirubin >1.5×ULN [see Contraindications (4), and Warnings and Precautions (5.2)]. Use caution when treating patients with mild hepatic impairment. If TORISEL must be given in patients with mild hepatic impairment (bilirubin >1–1.5×ULN or AST >ULN but bilirubin ≤ULN), reduce the dose of TORISEL to 15 mg/week [see Dosage and Administration (2.4)]. Because there is a need for dosage adjustment based upon hepatic function, assessment of AST and bilirubin levels is recommended before initiation of TORISEL and periodically thereafter.

10 OVERDOSAGE

There is no specific treatment for TORISEL intravenous overdose. TORISEL has been administered to patients with cancer in phase 1 and 2 trials with repeated intravenous doses as high as 220 mg/m^2. The risk of several serious adverse events, including thrombosis, bowel perforation, interstitial lung disease (ILD), seizure, and psychosis, is increased with doses of TORISEL greater than 25 mg.

11 DESCRIPTION

Temsirolimus, an inhibitor of mTOR, is an antineoplastic agent.

Temsirolimus is a white to off-white powder with a molecular formula of C56H87NO16 and a molecular weight of 1030.30. It is non-hygroscopic. Temsirolimus is practically insoluble in water and soluble in alcohol. It has no ionizable functional groups, and its solubility is independent of pH.

The chemical name of temsirolimus is (3S,6R,7E,9R,10R,12R,14S,15E,17E,19E,21S,23S,26R,27R,34aS)-9,10,12,13,14,21,22,23,24,25,26,27,32,33,34,34a-Hexadecahydro-9,27-dihydroxy-3-[(1R)-2-[(1S,3R,4R)-4-hydroxy-3-methoxycyclohexyl]-1-methylethyl]-10,21-dimethoxy-6,8,12,14,20,26-hexamethyl-23, 27-epoxy-3H-pyrido[2,1-c][1,4]oxaazacyclohentriacontine-1,5,11,28,29(4H,6H,31H)-pentone 4'-[2,2-bis(hydroxymethyl)propionate]; or Rapamycin, 42-[3-hydroxy-2-(hydroxymethyl)-2-methylpropanoate].

TORISEL (temsirolimus) injection, 25 mg/mL, is a clear, colorless to light yellow, non-aqueous, ethanolic, sterile solution. TORISEL (temsirolimus) injection requires two dilutions prior to intravenous infusion. TORISEL (temsirolimus) injection should be diluted only with the supplied DILUENT for TORISEL.

DILUENT for TORISEL is a sterile, non-aqueous solution that is supplied with TORISEL injection, as a kit.

TORISEL (temsirolimus) injection, 25 mg/mL:

Active ingredient: temsirolimus (25 mg/mL)

Inactive ingredients: dehydrated alcohol (39.5% w/v), dl-alpha-tocopherol (0.075% w/v), propylene glycol (50.3% w/v), and anhydrous citric acid (0.0025% w/v).

DILUENT for TORISEL:

Inactive ingredients: polysorbate 80 (40.0% w/v), polyethylene glycol 400 (42.8% w/v) and dehydrated alcohol (19.9% w/v).

After the TORISEL (temsirolimus) injection vial has been diluted with DILUENT for TORISEL, in accordance with the instructions in section 2.5, the solution contains 35.2% alcohol.

TORISEL (temsirolimus) injection and DILUENT for TORISEL are filled in clear glass vials with butyl rubber stoppers.

12 CLINICAL PHARMACOLOGY

12.1 Mechanism of Action

Temsirolimus is an inhibitor of mTOR (mammalian target of rapamycin). Temsirolimus binds to an intracellular protein (FKBP-12), and the protein-drug complex inhibits the activity of mTOR that controls cell division. Inhibition of mTOR activity resulted in a G1 growth arrest in treated tumor cells. When mTOR was inhibited, its ability to phosphorylate p70S6k and S6 ribosomal protein, which are downstream of mTOR in the PI3 kinase/AKT pathway was blocked. In in vitro studies using renal cell carcinoma cell lines, temsirolimus inhibited the activity of mTOR and resulted in reduced levels of the hypoxia-inducible factors HIF-1 and HIF-2 alpha, and the vascular endothelial growth factor.

12.2 Pharmacodynamics

Effects on Electrocardiogram: There were no clinically relevant QT changes observed at the recommended dose for TORISEL. In a randomized, single-blinded, crossover study, 58 healthy subjects received TORISEL 25 mg, placebo, and a single oral dose of moxifloxacin 400 mg. A supratherapeutic TORISEL dose was not studied in this randomized QT trial. The largest difference between the upper bound 2-sided 90% CI for the mean difference between TORISEL and placebo-corrected QT interval was less than 10 ms. In a different trial in 69 patients with a hematologic malignancy, TORISEL doses up to 175 mg were studied. No patient with a normal QTcF at baseline had an increase in QTcF >60 ms. Additionally, there were no patients with a QTcF interval greater than 500 ms.

12.3 Pharmacokinetics

Absorption

Following administration of a single 25 mg dose of TORISEL in patients with cancer, mean temsirolimus Cmax in whole blood was 585 ng/mL (coefficient of variation, CV = 14%), and mean AUC in blood was 1627 ng∙h/mL (CV = 26%). Typically Cmax occurred at the end of infusion. Over the dose range of 1 mg to 25 mg, temsirolimus exposure increased in a less than dose proportional manner while sirolimus exposure increased proportionally with dose. Following a single 25 mg intravenous dose in patients with cancer, sirolimus AUC was 2.7-fold that of temsirolimus AUC, due principally to the longer half-life of sirolimus.

Distribution

Following a single 25 mg intravenous dose, mean steady-state volume of distribution of temsirolimus in whole blood of patients with cancer was 172 liters. Both temsirolimus and sirolimus are extensively partitioned into formed blood elements.

Metabolism

Cytochrome P450 3A4 is the major isozyme responsible for the formation of five temsirolimus metabolites. Sirolimus, an active metabolite of temsirolimus, is the principal metabolite in humans following intravenous treatment. The remainder of the metabolites account for less than 10% of radioactivity in the plasma. In human liver microsomes temsirolimus was an inhibitor of CYP2D6 and 3A4. However, there was no effect observed in vivo when temsirolimus was administered with desipramine (a CYP2D6 substrate), and no effect is anticipated with substrates of CYP3A4 metabolism.

Elimination

Elimination is primarily via the feces. After a single IV dose of [^14C]-temsirolimus approximately 82% of total radioactivity was eliminated within 14 days, with 4.6% and 78% of the administered radioactivity recovered in the urine and feces, respectively. Following a single 25 mg dose of TORISEL in patients with cancer, temsirolimus mean (CV) systemic clearance was 16.2 (22%) L/h. Temsirolimus exhibits a bi-exponential decline in whole blood concentrations and the mean half-lives of temsirolimus and sirolimus were 17.3 hours and 54.6 hours, respectively.

Drug-Transport Systems - P-glycoprotein

Temsirolimus is a substrate of the efflux transporter P-glycoprotein (Pgp) in vitro. If TORISEL is administered with drugs that inhibit Pgp, increased concentrations of temsirolimus are likely and caution should be exercised.

In vitro, temsirolimus inhibited human Pgp (IC50 value of 2 µM). If TORISEL is administered with drugs that are substrates of Pgp, increased concentrations of the substrate drug are likely and caution should be exercised.

Effects of Age and Gender

In population pharmacokinetic-based data analyses, no relationship was apparent between drug exposure and patient age or gender.

Drug Interactions

Effect of Temsirolimus on CYP2D6 or CYP3A

The concentration of desipramine, a CYP2D6 substrate, was unaffected when 25 mg of temsirolimus was co-administered. No clinically significant effect is anticipated when 25 mg of temsirolimus is co-administered with agents that are metabolized by CYP2D6 or CYP3A.

13 NONCLINICAL TOXICOLOGY

13.1 Carcinogenesis, Mutagenesis, Impairment of Fertility

Carcinogenicity studies have not been conducted with temsirolimus. However, sirolimus, the major metabolite of temsirolimus in humans, was carcinogenic in mice and rats. The following effects were reported in mice and/or rats in the carcinogenicity studies conducted with sirolimus: lymphoma, hepatocellular adenoma and carcinoma, and testicular adenoma.

Temsirolimus was not genotoxic in a battery of in vitro (bacterial reverse mutation in Salmonella typhimurium and Escherichia coli, forward mutation in mouse lymphoma cells, and chromosome aberrations in Chinese hamster ovary cells) and in vivo (mouse micronucleus) assays.

In a fertility study in male rats, decreased number of pregnancies, decreased sperm concentration and motility, decreased reproductive organ weights, and testicular tubular degeneration were observed. These effects were observed at oral temsirolimus doses ≥3 mg/m^2/day (approximately 0.2-fold the human recommended intravenous dose). Fertility was absent at 30 mg/m^2/day.

In a fertility study in female rats, an increased incidence of pre- and post-implantation losses occurred at oral doses ≥4.2 mg/m^2/day (approximately 0.3-fold the human recommended intravenous dose), resulting in decreased numbers of live fetuses.

14 CLINICAL STUDIES

A phase 3, multi-center, three-arm, randomized, open-label study was conducted in previously untreated patients with advanced renal cell carcinoma (clear cell and non-clear cell histologies). The objectives were to compare Overall Survival (OS), Progression-Free Survival (PFS), Objective Response Rate (ORR), and safety in patients receiving IFN-α to those receiving TORISEL or TORISEL plus IFN-α. Patients in this study had 3 or more of 6 pre-selected prognostic risk factors (less than one year from time of initial renal cell carcinoma diagnosis to randomization, Karnofsky performance status of 60 or 70, hemoglobin less than the lower limit of normal, corrected calcium of greater than 10 mg/dL, lactate dehydrogenase >1.5 times the upper limit of normal, more than one metastatic organ site). Patients were stratified for prior nephrectomy status within three geographic regions and were randomly assigned (1:1:1) to receive IFN-α alone (n = 207), TORISEL alone (25 mg weekly; n = 209), or the combination arm (n = 210).

The ITT population for this interim analysis included 626 patients. Demographics were comparable between the three treatment arms with regard to age, gender, and race. The mean age of all groups was 59 years (range 23–86). Sixty-nine percent were male and 31% were female. The racial distribution for all groups was 91% White, 4% Black, 2% Asian, and 3% other. Sixty-seven percent of patients had a history of prior nephrectomy.

The median duration of treatment in the TORISEL arm was 17 weeks (range 1–126 weeks). The median duration of treatment on the IFN arm was 8 weeks (range 1–124 weeks).

There was a statistically significant improvement in OS (time from randomization to death) in the TORISEL 25 mg arm compared to IFN-α. The combination of TORISEL 15 mg and IFN-α did not result in a significant increase in OS when compared with IFN-α alone. Figure 1 is a Kaplan-Meier plot of OS in this study. The evaluations of PFS (time from randomization to disease progression or death) and ORR, were based on blinded independent radiologic assessment of tumor response. Efficacy results are summarized in Table 4.

Table 4 - Summary of Efficacy Results of TORISEL vs. IFN-α
Parameter | TORISEL n = 209 | IFN-α n = 207 | P-value [Based on log-rank test stratified by prior nephrectomy and region.] | Hazard Ratio (95% CI) [Based on Cox proportional hazard model stratified by prior nephrectomy and region.]
Median Overall Survival Months (95% CI) | 10.9 (8.6, 12.7) | 7.3 (6.1, 8.8) | 0.0078 [A comparison is considered statistically significant if the p-value is <0.0159 (O'Brien-Fleming boundary at 446 deaths).] | 0.73 (0.58, 0.92)
Median Progression-Free Survival Months (95% CI) | 5.5 (3.9, 7.0) | 3.1 (2.2, 3.8) | 0.0001 [Not adjusted for multiple comparisons.] | 0.66 (0.53, 0.81)
Overall Response Rate % (95% CI) | 8.6 (4.8, 12.4) | 4.8 (1.9, 7.8) | 0.1232 [Based on Cochran-Mantel-Haenszel test stratified by prior nephrectomy and region.] | NA
CI = confidence interval; NA = not applicable

Figure 1: Kaplan-Meier Curves for Overall Survival – TORISEL vs. IFN

15 REFERENCES

1. OSHA Hazardous Drugs. OSHA. https://www.osha.gov/SLTC/hazardousdrugs/index.html.

16 HOW SUPPLIED/STORAGE AND HANDLING

NDC 0008-1179-01 TORISEL (temsirolimus) injection, 25 mg/mL.

STORAGE AND HANDLING

Each kit is supplied in a single carton containing one single-use vial of 25 mg/mL of temsirolimus and one DILUENT vial which includes a deliverable volume of 1.8 mL, and must be stored at 2º–8º C (36º–46º F). Protect from light.

TORISEL is a cytotoxic drug. Follow applicable special handling and disposal procedures^1.

17 PATIENT COUNSELING INFORMATION

Allergic (Hypersensitivity/Infusion) Reactions

Patients should be informed of the possibility of serious allergic reactions, including anaphylaxis (including life threatening and fatal reactions), despite premedication with antihistamines, and to immediately report any facial swelling or difficulty breathing [see Warnings and Precautions (5.1)].

Increased Blood Glucose Levels

Patients are likely to experience increased blood glucose levels while taking TORISEL. This may result in the need for initiation of, or increase in the dose of, insulin and/or hypoglycemic agents. Patients should be directed to report any excessive thirst or frequency of urination to their physician [see Warnings and Precautions (5.3)].

Infections

Patients should be informed that they may be more susceptible to infections while being treated with TORISEL [see Warnings and Precautions (5.4)].

Interstitial Lung Disease

Patients should be warned of the possibility of developing interstitial lung disease, a chronic inflammation of the lungs, which may rarely result in death [see Warnings and Precautions (5.5)]. Patients, including those who are taking or have taken corticosteroids or immunosuppressive agents, should be directed to report promptly any new or worsening respiratory symptoms to their physician.

Increased Blood Triglycerides and/or Cholesterol

Patients are likely to experience elevated triglycerides and/or cholesterol during TORISEL treatment. This may require initiation of, or increase in the dose of, lipid-lowering agents [see Warnings and Precautions (5.6)].

Bowel Perforation

Patients should be warned of the possibility of bowel perforation. Patients should be directed to report promptly any new or worsening abdominal pain or blood in their stools [see Warnings and Precautions (5.7)].

Renal Failure

Patients should be informed of the risk of renal failure [see Warnings and Precautions (5.8)].

Wound Healing Complications

Patients should be advised of the possibility of abnormal wound healing if they have surgery within a few weeks of initiating therapy or during therapy [see Warnings and Precautions (5.9)].

Intracerebral Bleeding

Patients with CNS tumors and/or receiving anticoagulants should be informed of the increased risk of developing intracerebral bleeding (including fatal outcomes) while on TORISEL [see Warnings and Precautions (5.10)].

Proteinuria and Nephrotic Syndrome

Advise patients that treatment with TORISEL may require monitoring for proteinuria and nephrotic syndrome and to contact their health care provider for signs and symptoms of nephrotic syndrome [see Warnings and Precautions (5.11)].

Medications that can interfere with TORISEL

Some medicines can interfere with the breakdown or metabolism of TORISEL. In particular, patients should be directed to inform their physician if they are taking any of the following: Protease inhibitors, anti-epileptic medicines including carbamazepine, phenytoin, and barbiturates, St. John's Wort, rifampicin, rifabutin, nefazodone or selective serotonin re-uptake inhibitors used to treat depression, antibiotics or antifungal medicines used to treat infections [see Warnings and Precautions (5.12)].

Vaccinations

Patients should be advised that vaccinations may be less effective while being treated with TORISEL. In addition, the use of live vaccines, and close contact with those who have received live vaccines, while on TORISEL should be avoided [see Warnings and Precautions (5.14)].

Embryo-Fetal Toxicity

Advise pregnant women and females of reproductive potential that TORISEL can cause fetal harm. Advise females of reproductive potential to inform their healthcare provider of a known or suspected pregnancy [see Warnings and Precautions (5.15) and Use in Specific Populations (8.1)].

Advise females of reproductive potential to use effective contraception during treatment with TORISEL and for 3 months after receiving the last dose [see Use in Specific Populations (8.3)].

Advise males with female partners of reproductive potential to use effective contraception during treatment with TORISEL and for 3 months after receiving the last dose [see Use in Specific Populations (8.3)].

Lactation

Advise lactating women not to breastfeed during treatment with TORISEL and for 3 weeks after the last dose [see Use in Specific Populations (8.2)].

Infertility

Advise patients that male and female fertility may be compromised by treatment with TORISEL [see Use in Specific Populations (8.3) and Nonclinical Toxicology (13.1)].

Elderly Patients

Elderly patients should be advised that they may be more likely to experience certain adverse reactions including diarrhea, edema, and pneumonia [see Warnings and Precautions (5.16)].

This product's label may have been updated. For full prescribing information, please visit www.torisel.com.

LAB-0461-11.0

PRINCIPAL DISPLAY PANEL - 25 mg/mL Vial Label

TORISEL®
(temsirolimus) injection

25 mg/mL*

*each vial contains 0.2 mL overfill
MUST BE DILUTED
10 mg/mL after initial dilution
Single Use - Refrigerate
Cytotoxic: Handle with caution

Rx only

LOT / EXP.:

PRINCIPAL DISPLAY PANEL - 2.2 mL Vial Label

NDC 0008-1125-01
DILUENT
for TORISEL®

2.2 mL

Not for direct administration
Only for dilution of TORISEL
(temsirolimus) injection vial
Single Use - Refrigerate

LOT / EXP.:

PRINCIPAL DISPLAY PANEL - Kit Carton

NDC 0008-1179-01

Pfizer

TORISEL® Kit
(temsirolimus) injection

25 mg/mL*

*each vial contains 0.2 mL overfill

CONCENTRATED - Requires two dilutions
before administration

10 mg/mL after initial dilution
For intravenous infusion only

Each carton contains:
1 vial TORISEL® (temsirolimus) injection 25 mg/mL*
1 vial DILUENT for TORISEL®

Cytotoxic: Handle with caution

Refrigerate
Rx only